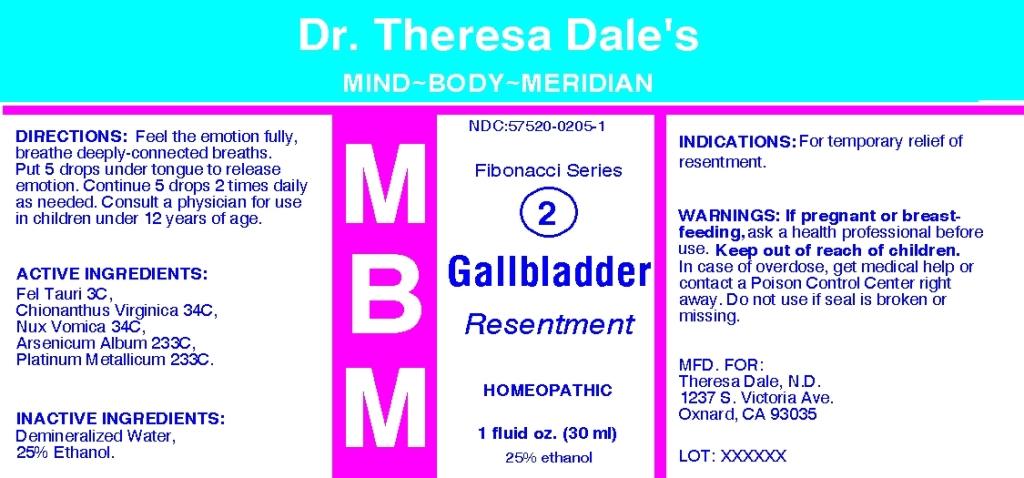 DRUG LABEL: MBM 2 Gallbladder
NDC: 57520-0205 | Form: LIQUID
Manufacturer: Apotheca Company
Category: homeopathic | Type: HUMAN OTC DRUG LABEL
Date: 20110502

ACTIVE INGREDIENTS: CHIONANTHUS VIRGINICUS BARK 34 [hp_C]/1 mL; STRYCHNOS NUX-VOMICA SEED 34 [hp_C]/1 mL; ARSENIC TRIOXIDE 233 [hp_C]/1 mL; PLATINUM 233 [hp_C]/1 mL; BOS TAURUS BILE 3 [hp_C]/1 mL
INACTIVE INGREDIENTS: WATER; ALCOHOL

MBM 2 Gallbladder

ACTIVE INGREDIENT

ACTIVE INGREDIENTS: Fel tauri 3C, Chionanthus virginica 34C, Nux vomica 34C, Arsenicum album 233C, Platinum metallicum 233C.

PURPOSE

INDICATIONS: For temporary relief of resentment.

WARNINGS

WARNINGS: If pregnant or breast-feeding, ask a health professional before use.

Keep out of reach of children. In case of overdose, get medical help or contact a Poison Control Center right away.

Do not use if seal is broken or missing.

DOSAGE AND ADMINISTRATION

DIRECTIONS: Feel the emotion fully, breathe deeply-connected breaths. Put 5 drops under tongue to release emotion. Continue 5 drops 2 times daily as needed. Consult a physician for use in children under 12 years of age.

INACTIVE INGREDIENTS: Demineralized water, 25% Ethanol

KEEP OUT OF REACH OF CHILDREN. In case of overdose, get medical help or contact a Poison Control Center right away.

INDICATIONS: For temporary relief of resentment.

QUESTIONS

MFD. FOR:

Theresa Dale, N.D.

1237 S Victoria Ave.

Oxnard, CA 93035

PACKAGE LABEL

Dr. Theresa Dale's

MIND-BODY-MERIDIAN

NDC: 57520-0205-1

MBM

Fibonacci Series

2

Gallbladder

Resentment

HOMEOPATHIC

1 fluid oz. (30 ml)